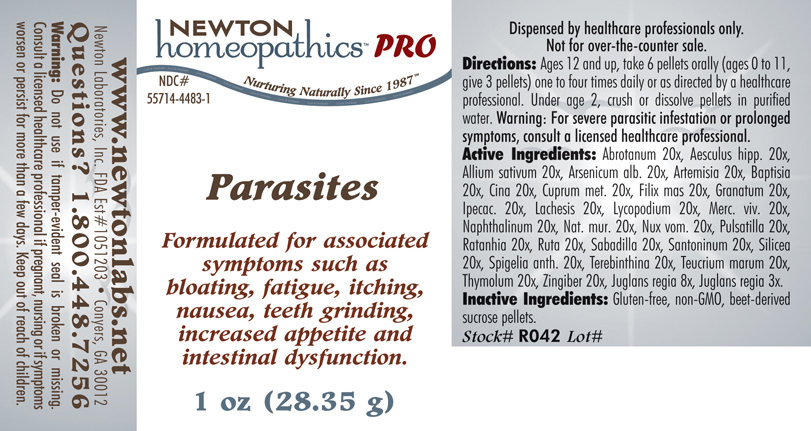 DRUG LABEL: Parasites 
NDC: 55714-4483 | Form: PELLET
Manufacturer: Newton Laboratories, Inc.
Category: homeopathic | Type: HUMAN PRESCRIPTION DRUG LABEL
Date: 20110601

ACTIVE INGREDIENTS: Artemisia Abrotanum Flowering Top 20 [hp_X]/1 g; Horse Chestnut 20 [hp_X]/1 g; Garlic 20 [hp_X]/1 g; Arsenic Trioxide 20 [hp_X]/1 g; Baptisia Tinctoria Root 20 [hp_X]/1 g; Artemisia Maritima Pre-flowering Top 20 [hp_X]/1 g; Copper 20 [hp_X]/1 g; Dryopteris Filix-mas Root 20 [hp_X]/1 g; Punica Granatum Root Bark 20 [hp_X]/1 g; Ipecac 20 [hp_X]/1 g; Lachesis Muta Venom 20 [hp_X]/1 g; Lycopodium Clavatum Spore 20 [hp_X]/1 g; Mercury 20 [hp_X]/1 g; Naphthalene 20 [hp_X]/1 g; Sodium Chloride 20 [hp_X]/1 g; Strychnos Nux-vomica Seed 20 [hp_X]/1 g; Pulsatilla Vulgaris 20 [hp_X]/1 g; Krameria Lappacea Root 20 [hp_X]/1 g; Ruta Graveolens Flowering Top 20 [hp_X]/1 g; Schoenocaulon Officinale Seed 20 [hp_X]/1 g; Santonin 20 [hp_X]/1 g; Silicon Dioxide 20 [hp_X]/1 g; Spigelia Anthelmia 20 [hp_X]/1 g; Turpentine Oil 20 [hp_X]/1 g; Teucrium Marum 20 [hp_X]/1 g; Thymol 20 [hp_X]/1 g; Ginger 20 [hp_X]/1 g; English Walnut 8 [hp_X]/1 g
INACTIVE INGREDIENTS: Sucrose

Parasites

INDICATIONS & USAGE SECTION

Parasites Formulated for associated symptoms such as bloating, fatigue, itching, nausea, teeth grinding, increased appetite and intestinal dysfunction.

DOSAGE & ADMINISTRATION SECTION

Directions: Ages 12 and up, take 6 pellets orally (ages 0 to 11, give 3 pellets) one to four times daily or as directed by a healthcare professional. Under age 2, crush or dissolve pellets in purified water. Warning: For severe parasitic infestation or prolonged symptoms, consult a licensed healthcare professional.

ACTIVE INGREDIENT SECTION

Abrotanum 20x, Aesculus hipp. 20x, Allium sativum 20x, Arsenicum alb. 20x, Artemisia 20x, Baptisia 20x, Cina 20x, Cuprum met. 20x, Filix mas 20x, Granatum 20x, Ipecac. 20x, Lachesis 20x, Lycopodium 20x, Merc. viv. 20x, Naphthalinum 20x, Nat. mur. 20x, Nux vom. 20x, Pulsatilla 20x, Ratanhia 20x, Ruta 20x, Sabadilla 20x, Santoninum 20x, Silicea 20x, Spigelia anth. 20x, Terebinthina 20x, Teucrium marum 20x, Thymolum 20x, Zingiber 20x, Juglans regia 8x, Juglans regia 3x.

PURPOSE SECTION

Formulated for associated symptoms such as bloating, fatigue, itching, nausea, teeth grinding, increased appetite and intestinal dysfunction.

INACTIVE INGREDIENT SECTION

Inactive Ingredients: Gluten-free, non-GMO, beet-derived sucrose pellets.

QUESTIONS? SECTION

www.newtonlabs.net Newton Laboratories, Inc. FDA Est # 1051203 - Conyers, GA 30012
Questions? 1.800.448.7256

WARNINGS SECTION

Warning: Do not use if tamper - evident seal is broken or missing. Consult a licensed healthcare professional if pregnant, nursing or if symptoms worsen or persist for more than a few days. Keep out of reach of children.

PREGNANCY OR BREAST FEEDING SECTION

Consult a licensed healthcare professional if pregnant, nursing or if symptoms worsen or persist for more than a few days.

KEEP OUT OF REACH OF CHILDREN SECTION

Keep out of reach of children